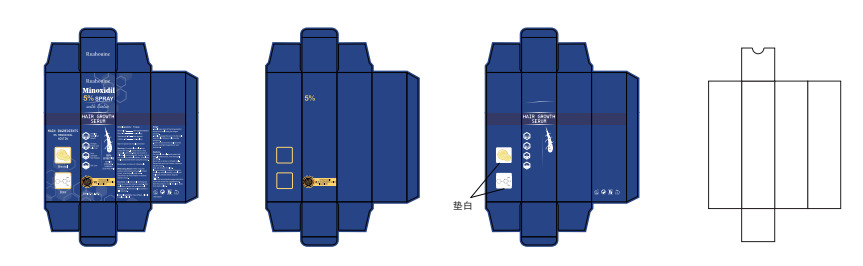 DRUG LABEL: Minoxidil 5% With Biotech Hair Growth Serum
NDC: 84355-002 | Form: SPRAY
Manufacturer: Guangzhou Binsi Clothing Co.,Ltd.
Category: otc | Type: HUMAN OTC DRUG LABEL
Date: 20240902

ACTIVE INGREDIENTS: MINOXIDIL 5 g/100 mL; CAFFEINE 0.2 g/100 mL; NIACINAMIDE 0.2 g/100 mL; BIOTIN 0.3 g/100 mL
INACTIVE INGREDIENTS: WATER; ALCOHOL; PROPYLENE GLYCOL

84355-002

Active Ingredient(s)

Minoxidil 5%

Biotin 0.3%

Niacinamide 0.2%

Caffeine 0.2%

Purpose

Hair regrowth treatment
Anti-hair loss
Hair regrowth
Anti-hair loss

Use

To regrow hair of scalp and beard

Warnings

Warnings: For external use only. Avoid contact with eyes. If contact occurs, rinse thoroughly
with water. Keep out of reach of Children. If you are pregnant, nursing, or have any
underlying medical condition, consult your healthcare provider before using the product.

Do not use

on broken or iritated scalp

WHEN USING

When Using Section: When using this product, avoid contact with eyes. If contact occurs,
rinse thoroughly with water. Discontinue use if any iritation or adverse reaction occurs.

STOP USE

If you feel unwell, please stop and consult a doctor.

keep out of reach of children.If swallowed, get medical help or contact PoisonControl Center right away.

Directions

Directions: Apply twice daily (morning and night) as a man and once as a woman. After
application, proceed with an active scalp massage for 3- 5 minutes until the product is
fully absorbed.

Other information

No data available

Inactive ingredients

INACTIVE INGREDIENTS:Aqua (Water), Alcohol, Propylene Glycol